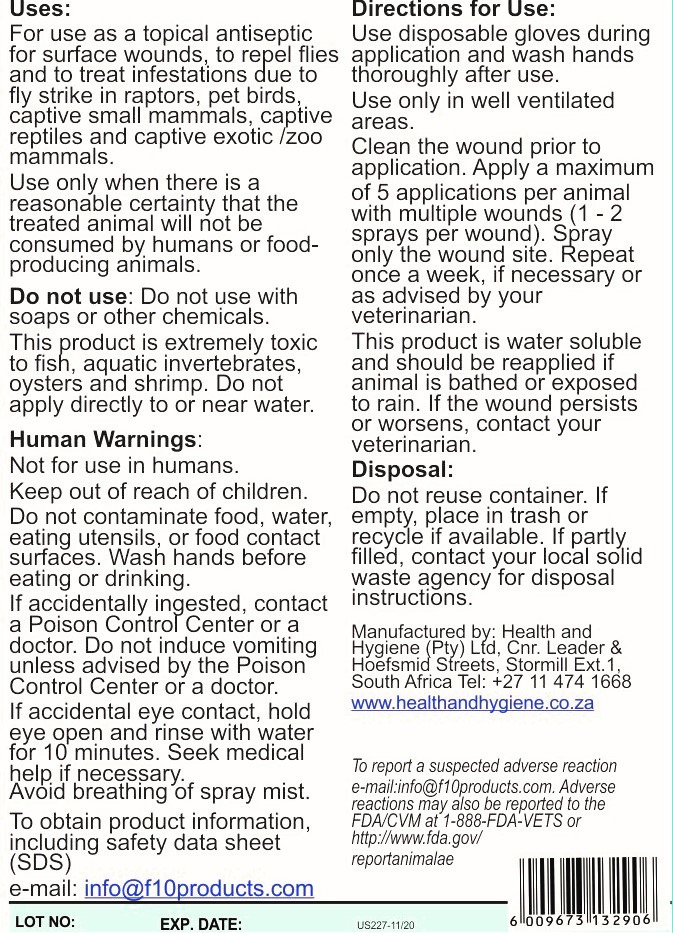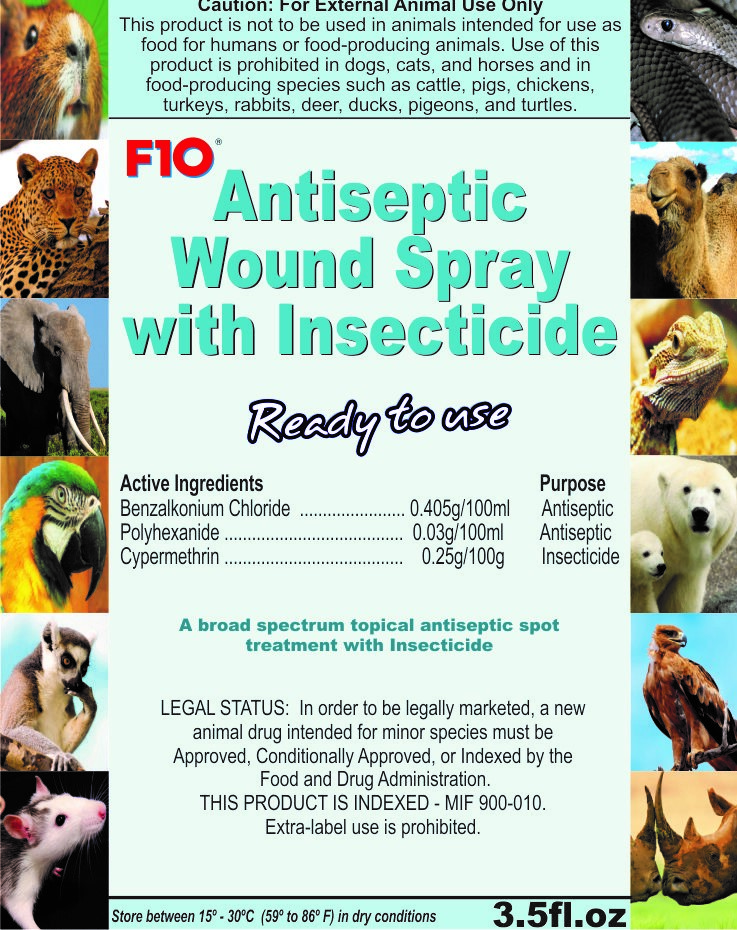 DRUG LABEL: F10
NDC: 86152-0101 | Form: SPRAY, METERED
Manufacturer: Health and Hygiene (Pty) Ltd
Category: animal | Type: OTC ANIMAL DRUG LABEL
Date: 20220126

ACTIVE INGREDIENTS: BENZALKONIUM CHLORIDE 0.4 g/100 mL; BIGUANIDE 0.03 g/100 mL; CYPERMETHRIN 0.25 g/100 mL

F10 Antiseptic Wound Spray with Insecticide

Human Warnings

Not for use in Humans. Keep out of reach of children

Uses

For use as a topical antiseptic for surface wounds, to repel flies and to treat infestations due to fly strike.

Directions of Use

Clean the wound prior to application. Apply a maximum of 5 applications per animal with multiple wounds (1-2 sprays per wound). Spray only the wound site. Repeat once a week if necessary or as advised by veterinarian. Product is water soluble and should be reapplied if animal is bathed or exposed to rain.

Packaging Label

Front Panel

US227-11 20 USA Wound Spray with Insecticide 100ml 3.5 fl FP.jpg

Packaging Label

Back Panel

US227-11 20 USA Wound Spray with Insecticide 100ml 3.5 fl BP.jpg